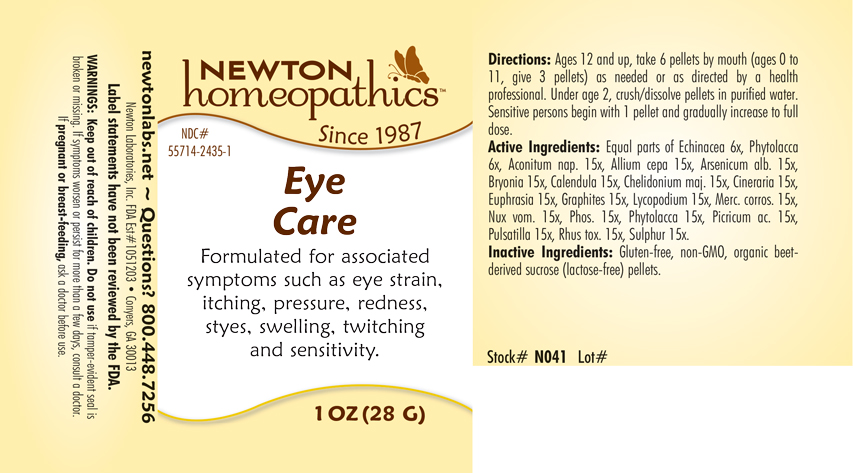 DRUG LABEL: Eye Care
NDC: 55714-2435 | Form: PELLET
Manufacturer: Newton Laboratories, Inc.
Category: homeopathic | Type: HUMAN OTC DRUG LABEL
Date: 20201125

ACTIVE INGREDIENTS: PICRIC ACID 15 [hp_X]/1 g; ACONITUM NAPELLUS 15 [hp_X]/1 g; ONION 15 [hp_X]/1 g; ARSENIC TRIOXIDE 15 [hp_X]/1 g; BRYONIA ALBA ROOT 15 [hp_X]/1 g; CALENDULA OFFICINALIS FLOWERING TOP 15 [hp_X]/1 g; CHELIDONIUM MAJUS 15 [hp_X]/1 g; JACOBAEA MARITIMA 15 [hp_X]/1 g; EUPHRASIA STRICTA 15 [hp_X]/1 g; GRAPHITE 15 [hp_X]/1 g; LYCOPODIUM CLAVATUM SPORE 15 [hp_X]/1 g; MERCURIC CHLORIDE 15 [hp_X]/1 g; STRYCHNOS NUX-VOMICA SEED 15 [hp_X]/1 g; PHOSPHORUS 15 [hp_X]/1 g; PHYTOLACCA AMERICANA ROOT 15 [hp_X]/1 g; PULSATILLA VULGARIS 15 [hp_X]/1 g; TOXICODENDRON PUBESCENS LEAF 15 [hp_X]/1 g; SULFUR 15 [hp_X]/1 g; ECHINACEA, UNSPECIFIED 6 [hp_X]/1 g
INACTIVE INGREDIENTS: SUCROSE

Eye 2435P

INDICATIONS & USAGE SECTION

Formulated for associated symptoms such as eye strain, itching, pressure, redness, styes, swelling, twitching and sensitivity.

DOSAGE & ADMINISTRATION SECTION

Directions: Ages 12 and up, take 6 pellets by mouth (ages 0 to 11, give 3 pellets) as needed or as directed by a health professional. Under age 2, crush or dissolve pellets in purified water. Sensitive persons begin with 1 pellet and gradually increase to full dose.

OTC - ACTIVE INGREDIENT SECTION

Equal parts of Echinacea 6x, Phytolacca 6x, Aconitum nap. 15x, Allium cepa 15x, Arsenicum alb. 15x, Bryonia 15x, Calendula 15x, Chelidonium maj. 15x, Cineraria 15x, Euphrasia 15x, Graphites 15x, Lycopodium 15x, Merc. corros. 15x, Nux vom. 15x, Phos. 15x, Phytolacca 15x, Picricum ac. 15x, Pulsatilla 15x, Rhus tox. 15x, Sulphur 15x.

INACTIVE INGREDIENT SECTION

Inactive Ingredients: Gluten-free, non-GMO, organic beet-derived sucrose (lactose-free) pellets.

QUESTIONS SECTION

newtonlabs.net – Questions? 800.448.7256

Newton Laboratories, Inc. FDA Est # 1051203 - Conyers, GA 30013

WARNINGS SECTION

WARNINGS: Keep out of reach of children. Do not use if tamper-evident seal is broken or missing. If symptoms worsen or persist for more than a few days, consult a doctor. If pregnant or breast-feeding, ask a doctor before use.

OTC - PREGNANCY OR BREAST FEEDING SECTION

If pregnant or breast-feeding, ask a doctor before use.

OTC - KEEP OUT OF REACH OF CHILDREN SECTION

Keep out of reach of children.